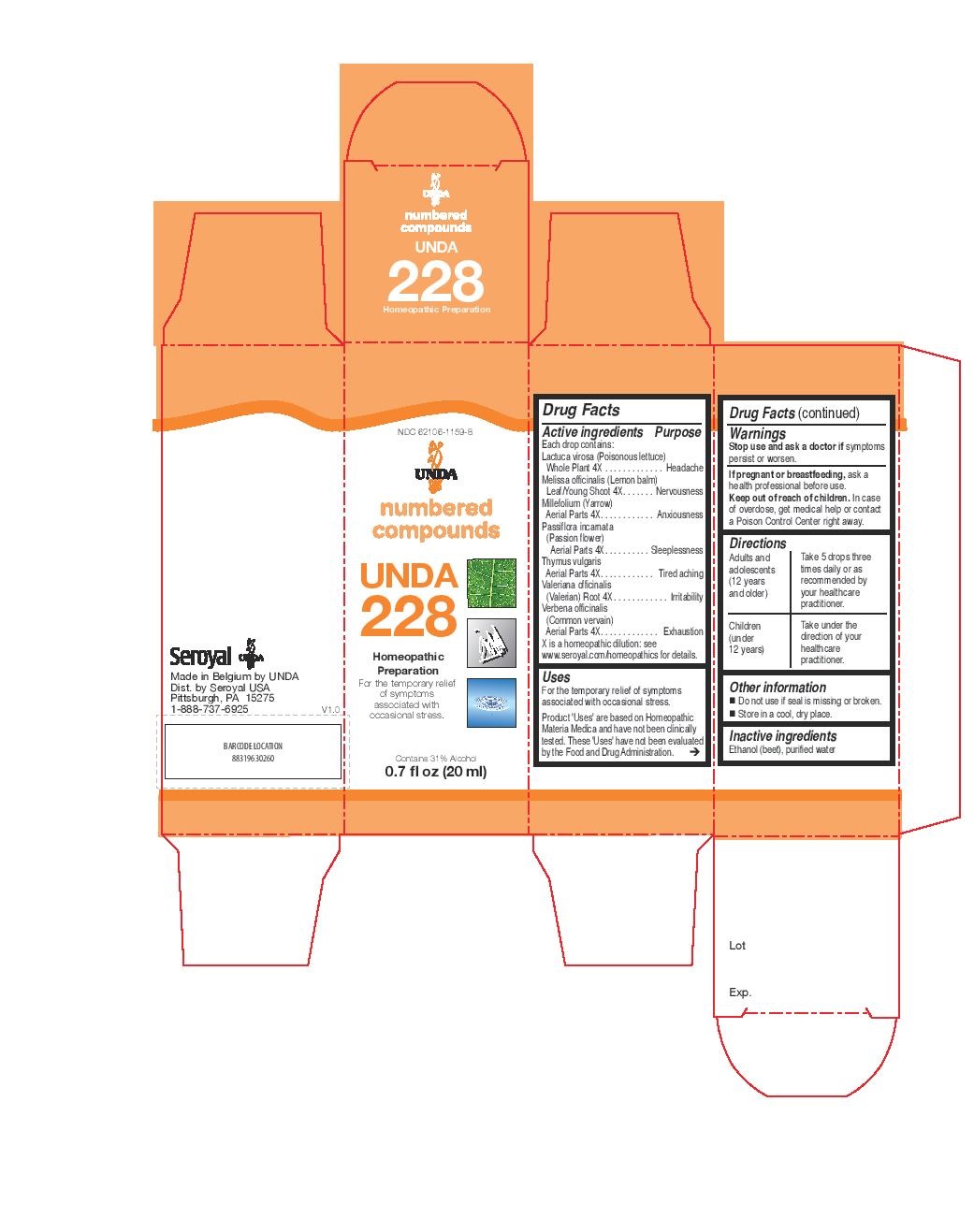 DRUG LABEL: Unda 228
NDC: 62106-1159 | Form: LIQUID
Manufacturer: Seroyal USA
Category: homeopathic | Type: HUMAN OTC DRUG LABEL
Date: 20221109

ACTIVE INGREDIENTS: MELISSA OFFICINALIS 4 [hp_X]/20 mL; ACHILLEA MILLEFOLIUM 4 [hp_X]/20 mL; LACTUCA VIROSA 4 [hp_X]/20 mL; THYME 4 [hp_X]/20 mL; PASSIFLORA INCARNATA FLOWERING TOP 4 [hp_X]/20 mL; VERBENA OFFICINALIS 4 [hp_X]/20 mL; VALERIAN 4 [hp_X]/20 mL
INACTIVE INGREDIENTS: ALCOHOL; WATER

Unda 228

Active ingredients
Each drop contains:
Lactuca virosa (Poisonous lettuce) Whole Plant 4X
Melissa officinalis (Lemon balm) Leaf/Young Shoot 4X
Millefolium (Yarrow) Aerial Parts 4X
Passiflora incarnata (Passion flower) Aerial Parts 4X
Thymus vulgaris Aerial Parts 4X
Valeriana officinalis (Valerian) Root 4X
Verbena officinalis (Common vervain) Aerial Parts 4X.

Uses
For the temporary relief of symptoms associated with occasional stress.

Warnings
Stop use and ask a doctor if symptoms persist or worsen.
If pregnant or breastfeeding, ask a health professional before use.
Keep out of reach of children. In case of overdose, get medical help or contact
a Poison Control Center right away.

PREGNANCY OR BREAST FEEDING

If pregnant or breastfeeding, ask a health professional before use.

Keep out of reach of children.

OVERDOSAGE

In case of overdose, get medical help or contact a
Poison Control Center right away.

Stop use and ask a doctor if symptoms persist or worsen.

Inactive Ingredients:

Ethanol (beet),
purified water

Other information
Do not use if seal is missing or broken.
Store in a cool, dry place.

Directions:

Adults and adolescents (12 years and older)

Take 5 drops three times daily or as recommended by your healthcare practitioner.

Children (under 12 years)

Take under the direction of your healthcare practitioner.

Uses
For the temporary relief of symptoms associated with occasional stress.

Directions:

Adults and adolescents (12 years and older)

Take 5 drops three times daily or as recommended by your healthcare practitioner.

Children (under 12 years)

Take under the direction of your healthcare practitioner.

PACKAGE LABEL

NDC 62106-1159-8

UNDA

numbered compounds

UNDA 228

Homeopathic Preparation

For the temporary relief
of symptomsassociated with
occasional stress.

Contains 31% Alcohol

0.7 fl oz (20 ml)